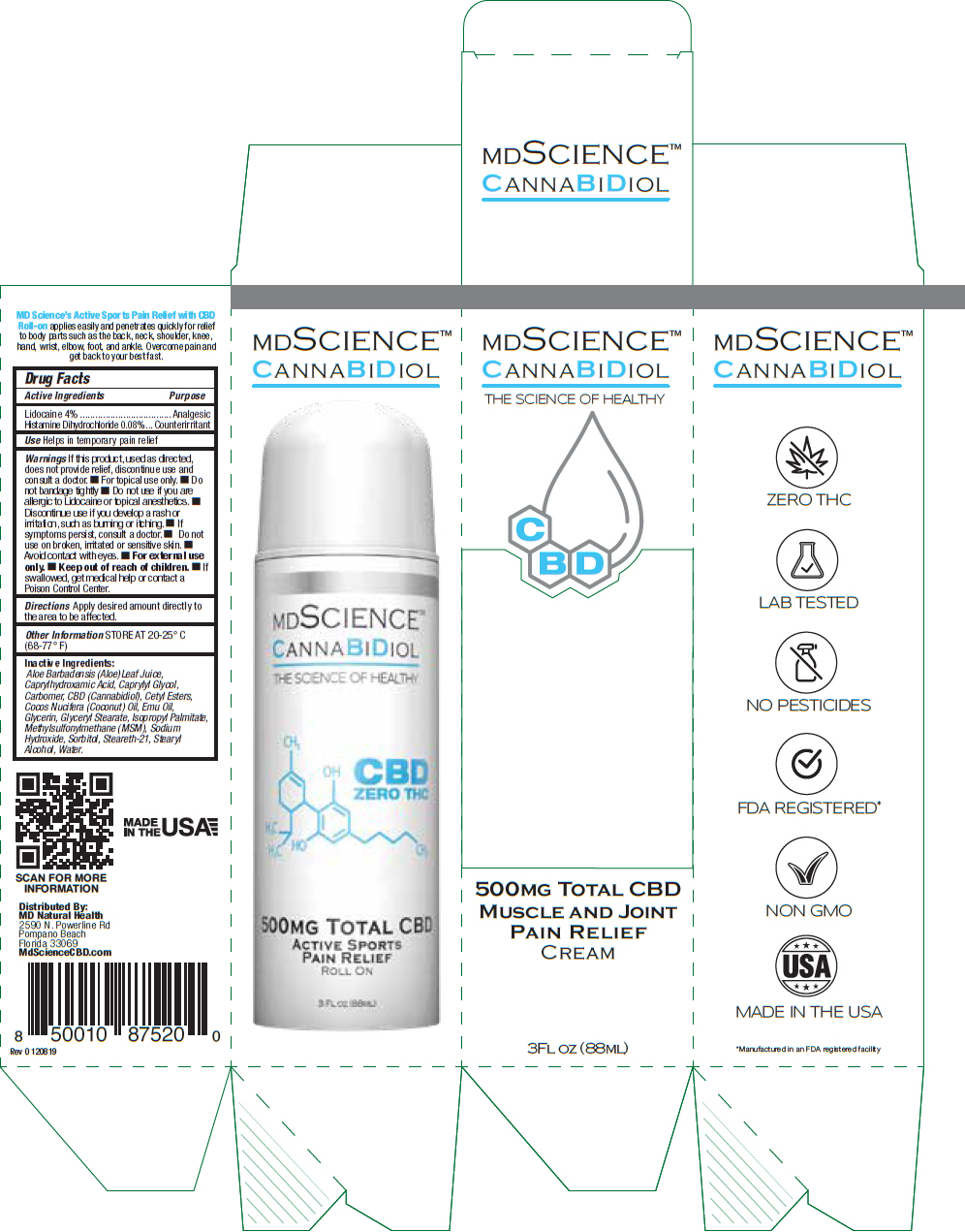 DRUG LABEL: MD SCIENCE CANNABIDIOL
NDC: 73615-103 | Form: CREAM
Manufacturer: MD NATURAL HEALTH LLC
Category: otc | Type: HUMAN OTC DRUG LABEL
Date: 20200210

ACTIVE INGREDIENTS: Lidocaine 37.8 mg/1 mL; Histamine Dihydrochloride 0.041 mg/1 mL
INACTIVE INGREDIENTS: Aloe Vera Leaf; Caprylhydroxamic Acid; Caprylyl Glycol; Carbomer Homopolymer Type C (Allyl Pentaerythritol Crosslinked); Cannabidiol; Cetyl Esters Wax; Coconut Oil; Emu Oil; Glycerin; Glyceryl Monostearate; Isopropyl Palmitate; Dimethyl Sulfone; Sodium Hydroxide; Sorbitol; Steareth-21; Stearyl Alcohol

MD SCIENCE™ CANNABIDIOL

Drug Facts

ACTIVE INGREDIENT

Active Ingredients | Purpose
Lidocaine 4% | Analgesic
Histamine Dihydrochloride 0.08% | Counterirritant

Use

Helps in temporary pain relief

Warnings

If this product, used as directed, does not provide relief, discontinue use and consult a doctor.

- For topical use only.
- Do not bandage tightly

- Do not use if you are allergic to Lidocaine or topical anesthetics.

STOP USE

- Discontinue use if you develop a rash or irritation, such as burning or itching.

- If symptoms persist, consult a doctor.

- Do not use on broken, irritated or sensitive skin.

- Avoid contact with eyes.
- For external use only.

- Keep out of reach of children.
- If swallowed, get medical help or contact a Poison Control Center.

Directions

Apply desired amount directly to the area to be affected.

Other Information

STORE AT 20-25° C (68-77° F)

Inactive Ingredients

Aloe Barbadensis (Aloe)Leaf Juice, Caprylhydroxamic Acid, Caprylyl Glycol, Carbomer, CBD (Cannabidiol), Cetyl Esters, Cocos Nucifera (Coconut) Oil, Emu Oil, Glycerin, Glyceryl Stearate, Isopropyl Palmitate, Methylsulfonylmethane (MSM), Sodium Hydroxide, Sorbitol, Steareth-21, Stearyl Alcohol, Water.

Distributed By:
MD Natural Health
2590 N. Powerline Rd
Pompano Beach
Florida 33069

PRINCIPAL DISPLAY PANEL - 88 ML Bottle Box

MDSCIENCE™
CANNABIDIOL
THE SCIENCE OF HEALTHY

CBD

500MG TOTAL CBD
MUSCLE AND JOINT
PAIN RELIEF
CREAM

3FL OZ (88ML)